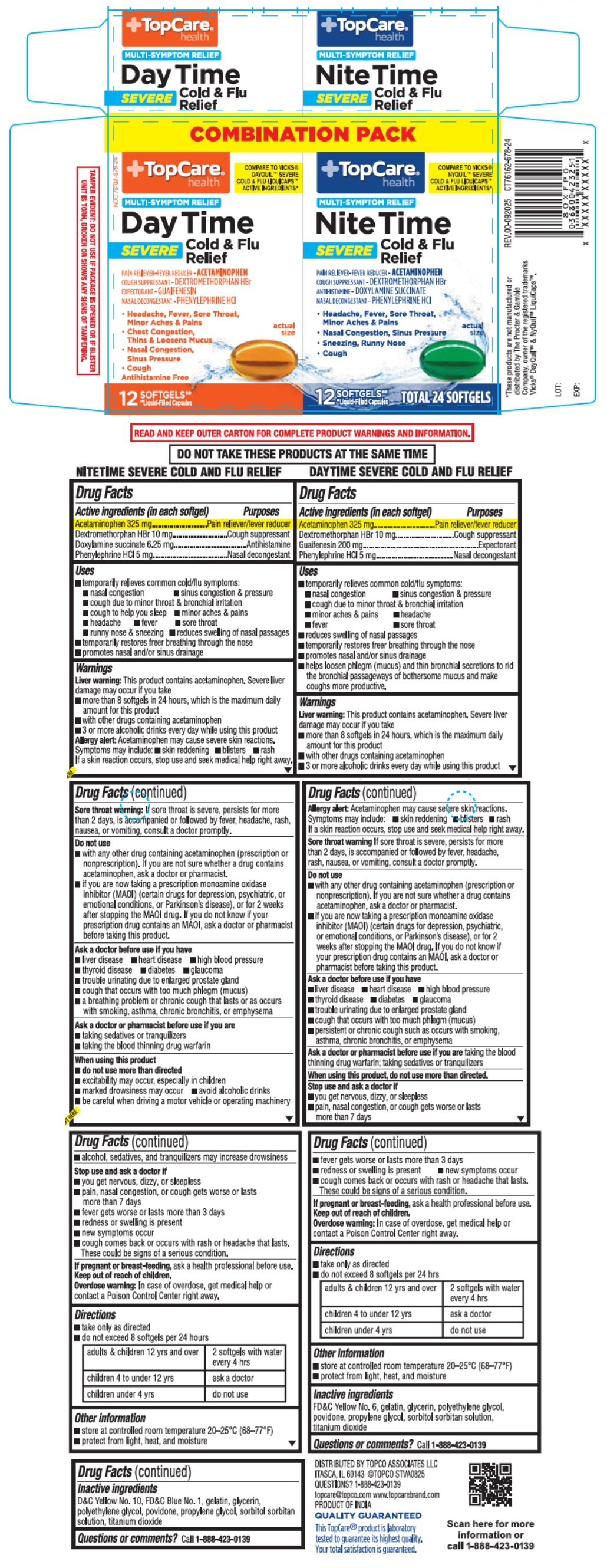 DRUG LABEL: COMBINATION PACK TopCare health DayTime SEVERE and NiteTime SEVERE Cold and Flu Relief SOFTGELS - 24 ct
NDC: 76162-678 | Form: KIT | Route: ORAL
Manufacturer: Topco Associates LLC
Category: otc | Type: HUMAN OTC DRUG LABEL
Date: 20251219

ACTIVE INGREDIENTS: ACETAMINOPHEN 325 mg/1 1; DEXTROMETHORPHAN HYDROBROMIDE 10 mg/1 1; GUAIFENESIN 200 mg/1 1; PHENYLEPHRINE HYDROCHLORIDE 5 mg/1 1; ACETAMINOPHEN 325 mg/1 1; DEXTROMETHORPHAN HYDROBROMIDE 10 mg/1 1; DOXYLAMINE SUCCINATE 6.25 mg/1 1; PHENYLEPHRINE HYDROCHLORIDE 5 mg/1 1
INACTIVE INGREDIENTS: FD&C YELLOW NO. 6; GELATIN, UNSPECIFIED; GLYCERIN; POLYETHYLENE GLYCOL, UNSPECIFIED; POVIDONE, UNSPECIFIED; PROPYLENE GLYCOL; SORBITOL; SORBITAN; TITANIUM DIOXIDE; D&C YELLOW NO. 10; FD&C BLUE NO. 1; GELATIN, UNSPECIFIED; GLYCERIN; POLYETHYLENE GLYCOL, UNSPECIFIED; POVIDONE, UNSPECIFIED; PROPYLENE GLYCOL; SORBITOL; SORBITAN; TITANIUM DIOXIDE

COMBINATION PACK TopCare® health DayTime SEVERE and NiteTime SEVERE Cold & Flu Relief SOFTGELS

DAYTIME SEVERE COLD AND FLU RELIEF

Drug Facts

Active ingredients (in each softgel)

Acetaminophen 325 mg
Dextromethorphan HBr 10 mg
Guaifenesin 200 mg
Phenylephrine HCl 5 mg

Purposes

Pain reliever/fever reducer
Cough suppressant
Expectorant
Nasal decongestant

Uses

• temporarily relieves common cold/flu symptoms:
• nasal congestion • sinus congestion & pressure
• cough due to minor throat & bronchial irritation
• minor aches & pains • head ache
• fever • sore throat
• reduces swelling of nasal passages
• temporarily restores freer breathing through the nose
• promotes nasal and/or sinus drainage
• helps loosen phlegm (mucus) and thin bronchial secretions to rid the bronchial passageways of bothersome mucus and make coughs more productive.

Warnings

Liver warning: This product contains acetaminophen. Severe liver damage may occur if you take
• more than 8 softgels in 24 hours, which is the maximum daily amount for this product
• with other drugs containing acetaminophen
• 3 or more alcoholic drinks every day while using this product
Allergy alert: Acetaminophen may cause severe skin reactions.
Symptoms may include: • skin reddening • blisters • rash
If a skin reaction occurs, stop use and seek medical help right away.
Sore throat warning If sore throat is severe, persists for more than 2 days, is accompanied or followed by fever, headache, rash, nausea, or vomiting, consult a doctor promptly.

Do not use
• with any other drug containing acetaminophen (prescription or nonprescription). If you are not sure whether a drug contains acetaminophen, ask a doctor or pharmacist.
• if you are now taking a prescription monoamine oxidase inhibitor (MAOI) (certain drugs for depression, psychiatric, or emotional conditions, or Parkinson's disease), or for 2 weeks after stopping the MAOI drug. If you do not know if your prescription drug contains an MAOI, ask a doctor or pharmacist before taking this product.

Ask a doctor before use if you have
• liver disease • heart disease • high blood pressure
• thyroid disease • diabetes • glaucoma
• trouble urinating due to enlarged prostate gland
• cough that occurs with too much phlegm (mucus)
• persistent or chronic cough such as occurs with smoking, asthma, chronic bronchitis or emphysema

Ask a doctor or pharmacist before use if you are taking the blood thinning drug warfarin; taking sedatives or tranquilizers

When using this product, do not use more than directed.

Stop use and ask a doctor if
• you get nervous, dizzy, or sleepless
• pain, nasal congestion, or cough gets worse or lasts more than 7 days
• fever gets worse or lasts more than 3 days
• redness or swelling is present • new symptoms occur
• cough comes back or occurs with rash or headache that lasts.
These could be signs of a serious condition.

If pregnant or breast-feeding, ask a health professional before use.

Keep out of reach of children.
Overdose warning: In case of overdose, get medical help or contact a Poison Control Center right away.

Directions

• take only as directed
• do not exceed 8 softgels per 24 hrs

adults & children 12 yrs and over | 2 softgels with water every 4 hrs
children 4 to under 12 yrs | ask a doctor
children under 4 yrs | do not use

Other information

• store at controlled room temperature between 20-25°C (68-77°F)
• protect from light, heat, and moisture

Inactive ingredients

FD&C Yellow No. 6, gelatin, glycerin, polyethylene glycol, povidone, propylene glycol, sorbitol sorbitan solution, titanium dioxide

Questions or comments?

Call 1-888-423-0139

NITETIME SEVERE COLD AND FLU RELIEF

Drug Facts

Active ingredients (in each softgel)

Acetaminophen 325 mg
Dextromethorphan HBr 10 mg
Doxylamine succinate 6.25 mg
Phenylephrine HCl 5 mg

Purposes

Pain reliever/fever reducer
Cough suppressant
Antihistamine
Nasal decongestant

Uses

• temporarily relieves common cold/flu symptoms:
• nasal congestion • sinus congestion & pressure
• cough due to minor throat & bronchial irritation
• cough to help you sleep • minor aches & pains
• headache • fever • sore throat
• runny nose & sneezing • reduces swelling of nasal passages
• temporarily restores freer breathing through the nose
• promotes nasal and/or sinus drainage

Warnings

Liver warning: This product contains acetaminophen. Severe liver damage may occur if you take
• more than 8 softgels in 24 hours, which is the maximum daily amount for this product
• with other drugs containing acetaminophen
• 3 or more alcoholic drinks every day while using this product
Allergy alert: Acetaminophen may cause severe skin reactions.
Symptoms may include: • skin reddening • blisters • rash
If a skin reaction occurs, stop use and seek medical help right away.
Sore throat warning: If sore throat is severe, persists for more than 2 days, is accompanied or followed by fever, headache, rash, nausea, or vomiting, consult a doctor promptly.

Do not use
• with any other drug containing acetaminophen (prescription or nonprescription). If you are not sure whether a drug contains acetaminophen, ask a doctor or pharmacist.
• if you are now taking a prescription monoamine oxidase inhibitor (MAOI) (certain drugs for depression, psychiatric, or emotional conditions, or Parkinson’s disease), or for 2 weeks after stopping the MAOI drug. If you do not know if your prescription drug contains an MAOI, ask a doctor or pharmacist before taking this product.

Ask a doctor before use if you have
• liver disease • heart disease • high blood pressure
• thyroid disease • diabetes • glaucoma
• trouble urinating due to enlarged prostate gland
• cough that occurs with too much phlegm (mucus)
• a breathing problem or chronic cough that lasts or as occurs with smoking, asthma, chronic bronchitis, or emphysema

Ask a doctor or pharmacist before use if you are
• taking sedatives or tranquilizers
• taking the blood thinning drug warfarin

When using this product
• do not use more than directed
• excitability may occur, especially in children
• marked drowsiness may occur • avoid alcoholic drinks
• be careful when driving a motor vehicle or operating machinery
• alcohol, sedatives, and tranquilizers may increase drowsiness

Stop use and ask a doctor if
• you get nervous, dizzy, or sleepless
• pain, nasal congestion, or cough gets worse or lasts more than 7 days
• fever gets worse or lasts more than 3 days
• redness or swelling is present
• new symptoms occur
• cough comes back or occurs with rash or headache that lasts.
These could be signs of a serious condition.

If pregnant or breast-feeding, ask a health professional before use.

Keep out of reach of children.
Overdose warning: In case of overdose, get medical help or contact a Poison Control Center right away.

Directions

• take only as directed
• do not exceed 8 softgels per 24 hours

adults & children 12 yrs and over | 2 softgels with water every 4 hrs
children 4 to under 12 yrs | ask a doctor
children under 4 yrs | do not use

Other information

• store at controlled room temperature between 20-25°C (68-77°F)
• protect from light, heat, and moisture

Inactive ingredients

D&C Yellow No. 10, FD&C Blue No. 1, gelatin, glycerin, polyethylene glycol, povidone, propylene glycol, sorbitol sorbitan solution, titanium dioxide

Questions or comments?

Call 1-888-423-0139

COMPARE TO VICKS® DAYQUIL™ SEVERE COLD & FLU LIQUICAPS™ ACTIVE INGREDIENTS*

MULTI-SYMPTOM RELIEF

Antihistamine Free

COMPARE TO VICKS® NYQUIL™ SEVERE COLD & FLU LIQUICAPS™ ACTIVE INGREDIENTS*

*These products are not manufactured or distributed by The Procter & Gamble Company, owner of the registered trademarks Vicks® DayQuil™ & NyQuil™ LiquiCaps™.

READ AND KEEP OUTER CARTON FOR COMPLETE PRODUCT WARNINGS AND INFORMATION

DO NOT TAKE THESE PRODUCTS AT THE SAME TIME

TAMPER EVIDENT: DO NOT USE IF PACKAGE IS OPENED OR IF BLISTER UNIT IS TORN, BROKEN OR SHOWS ANY SIGNS OF TAMPERING.

DISTRIBUTED BY TOPCO ASSOCIATES LLC
ITASCA, IL 60143 ©TOPCO STVA0825

topcare@topco.com www.topcarebrand.com
PRODUCT OF INDIA

QUALITY GUARANTEED

This Topcare® product is laboratory tested to guarantee its highest quality. Your total satisfaction is guaranteed.